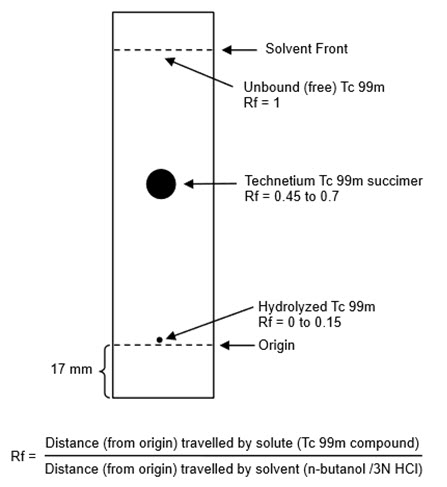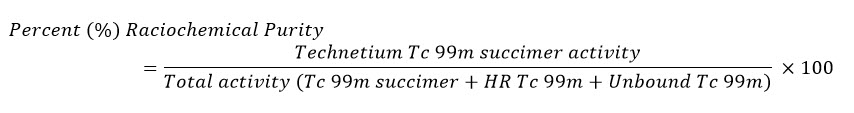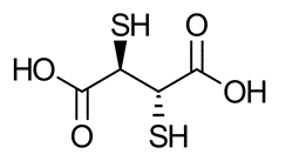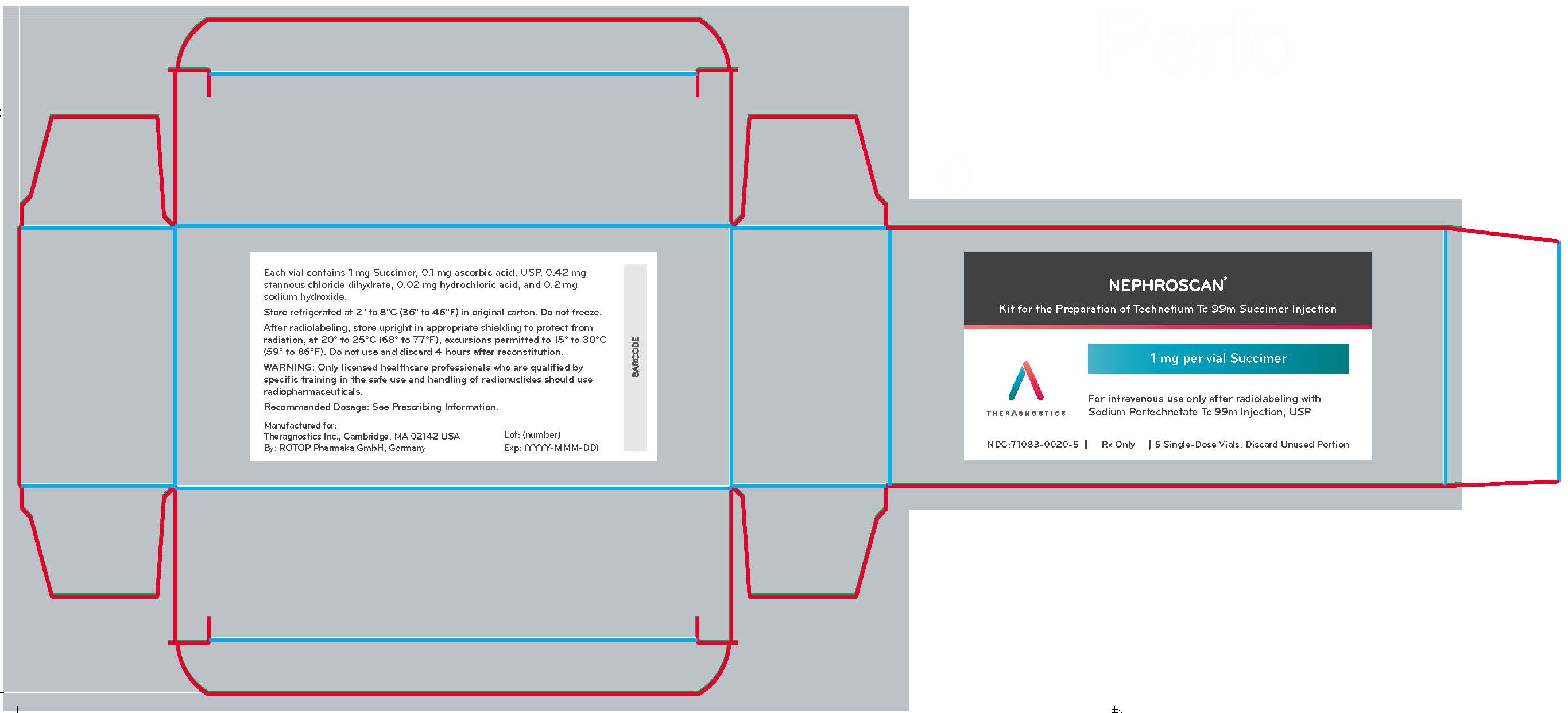 DRUG LABEL: NephroScan
NDC: 71083-0020 | Form: INJECTION, POWDER, LYOPHILIZED, FOR SOLUTION
Manufacturer: Theragnostics Inc
Category: prescription | Type: HUMAN PRESCRIPTION DRUG LABEL
Date: 20240929

ACTIVE INGREDIENTS: SUCCIMER 1 mg/1 1
INACTIVE INGREDIENTS: STANNOUS CHLORIDE; ascorbic acid; sodium hydroxide; hydrochloric acid

HIGHLIGHTS OF PRESCRIBING INFORMATION

These highlights do not include all the information needed to use NEPHROSCAN® safely and effectively. See full prescribing information for NEPHROSCAN.
NEPHROSCAN (kit for the preparation of technetium Tc 99m succimer injection), for intravenous use
Initial U.S. Approval: 1982

1 INDICATIONS AND USAGE

NEPHROSCAN, after radiolabeling with technetium Tc 99m, is a radioactive diagnostic agent indicated for use as an aid in the scintigraphic evaluation of renal parenchymal disorders in adults and pediatric patients including term neonates. (1)

2 DOSAGE AND ADMINISTRATION

- Instruct patients to drink a sufficient amount of water before administration and to continue to drink and to void frequently following administration (2.2)
- The recommended amount of radioactivity by intravenous injection (bolus) is:
  - For adults: 74 MBq to 222 MBq (2 mCi to 6 mCi) (2.3)
  - For pediatric patients: 1.85 MBq/kg (0.05 mCi/kg) of body weight with a range of 19 MBq to 74 MBq (0.5 mCi to 2 mCi). (2.3)
- Begin image acquisition 1 hour to 4 hours after administration (2.7)
- Delay imaging up to 6 hours to 24 hours in patients with severely reduced eGFR (2.7)
- See Full Prescribing Information for radiation safety, drug preparation, administration, and radiation dosimetry information (2.1, 2.4, 2.5, 2.6, 2.8)

3 DOSAGE FORMS AND STRENGTHS

For Injection: NEPHROSCAN contains 1 mg succimer as a white-yellowish to off-white lyophilized powder in a single dose vial. Upon radiolabeling with technetium Tc 99m, it provides a clear, colorless solution containing up to 1,480 MBq (40 mCi) technetium Tc 99m succimer in approximately 5 mL volume at calibration time. (3)

4 CONTRAINDICATIONS

None (4)

5 WARNINGS AND PRECAUTIONS

- Hypersensitivity Reactions: Have appropriate instruments and medications necessary for immediate treatment of allergic reactions and monitor patients for hypersensitivity reactions during and after administration (5.1)
- Radiation risks: Ensure safe handling to minimize radiation exposure to patients and health care workers (5.2)
- Risk in Patients with Advanced Renal Failure: Image interpretation may be affected as the kidneys may not absorb technetium Tc 99m succimer. (5.3)

6 ADVERSE REACTIONS

The following adverse reactions have been reported: urticaria, rash, pruritus, erythema, syncope, fever, and nausea. (6)

To report SUSPECTED ADVERSE REACTIONS, contact Theragnostics, Inc., at 1-888-286-3848 or FDA at 1-800-FDA-1088 or www.fda.gov/medwatch.

8 USE IN SPECIFIC POPULATIONS

Lactation: Temporarily discontinue breastfeeding. A lactating woman should pump and discard breastmilk for at least 24 hours after Technetium Tc 99m Succimer Injection administration. (8.2)

FULL PRESCRIBING INFORMATION

1 INDICATIONS AND USAGE

NEPHROSCAN, after radiolabeling with technetium Tc 99m, is indicated for use as an aid in the scintigraphic evaluation of renal parenchymal disorders in adult and pediatric patients including term neonates.

2 DOSAGE AND ADMINISTRATION

2.1 Radiation Safety – Drug Handling

After radiolabeling, handle Technetium Tc 99m Succimer Injection with appropriate safety measures to minimize radiation exposure [see Warnings and Precautions (5.2)]. Use waterproof gloves, effective radiation shielding, and other appropriate safety measures when preparing and handling Technetium Tc 99m Succimer Injection.

Radiopharmaceuticals should be used by or under the control of physicians who are qualified by specific training and experience in the safe use and handling of radionuclides, and whose experience and training have been approved by the appropriate governmental agency authorized to license the use of radionuclides.

2.2 Patient Preparation

Instruct patients to drink a sufficient amount of water to ensure adequate hydration prior to administration of Technetium Tc 99m Succimer Injection and to continue to drink and void frequently following administration to reduce radiation exposure [see Warnings and Precautions (5.2)].

2.3 Recommended Dosage

Adults

The recommended amount of radioactivity of Technetium Tc 99m Succimer Injection for renal parenchymal imaging in adults is 74 MBq to 222 MBq (2 mCi to 6 mCi) by intravenous injection (bolus).

Pediatric Patients

The recommended amount of radioactivity of Technetium Tc 99m Succimer Injection for renal parenchymal imaging in pediatric patients is 1.85 MBq/kg (0.05 mCi/kg) of body weight with a range of 19 MBq to 74 MBq (0.5 mCi to 2 mCi) by intravenous injection (bolus). Weight based pediatric dosing is shown in Table 1.

Table 1 Recommended Radioactivity of Technetium Tc 99m Succimer Injection for Pediatric Patients by Body Weight
Body Weight (kg) | Recommended Radioactivity MBq (mCi) | Body Weight (kg) | Recommended Radioactivity MBq (mCi)
less than 11 kg | 19 MBq (0.5 mCi) | 25 to 26 | 49 MBq (1.3 mCi)
11 to 12 | 21 MBq (0.6 mCi) | 27 to 28 | 52 MBq (1.4 mCi)
13 to 14 | 26 MBq (0.7 mCi) | 29 to 30 | 56 MBq (1.5 mCi)
15 to 16 | 30 MBq (0.8 mCi) | 31 to 32 | 59 MBq (1.6 mCi)
17 to 18 | 33 MBq (0.9 mCi) | 33 to 34 | 63 MBq (1.7 mCi)
19 to 20 | 37 MBq (1 mCi) | 35 to 36 | 67 MBq (1.8 mCi)
21 to 22 | 41 MBq (1.1 mCi) | 37 to 38 | 70 MBq (1.9 mCi)
23 to 24 | 44 MBq (1.2 mCi) | 39 or greater | 74 MBq (2 mCi)

2.4 Drug Preparation

Prepare Technetium Tc 99m Succimer Injection according to the following procedure using asceptic technique:

1. Wear waterproof gloves.
2. Place the kit vial in lead shielding and disinfect the stopper (allow disinfectant to dry).
3. Use a sterile syringe to transfer 5 mL sodium pertechnetate Tc 99m injection obtained from a technetium Tc 99m generator with a maximum activity of 1,480 MBq (40 mCi) to the vial. The volume of sodium pertechnetate Tc 99m injection may be adjusted to 5 mL prior to adding to the kit vial using 0.9% sodium chloride injection, USP.
4. Use the same syringe to withdraw the appropriate gas volume from the vial for pressure compensation.
5. Lightly shake the vial to completely dissolve the powder. Ensure the stopper is well moistened.
6. Incubate the vial for 10 minutes at controlled room temperature 20°C to 25°C (68°F to 77°F).
7. Measure the product activity in a dose calibrator; complete the radiolabeled product vial label and affix to the vial shield.
8. Check radiochemical purity according to the method in 2.5 Radiochemical Purity Determination [see Dosage and Administration (2.5)].
9. Use Technetium Tc 99m Succimer Injection within 4 hours and store at controlled room temperature 20°C to 25°C (68°F to 77°F); excursions permitted to 15°C to 30°C (59°F to 86°F).

2.5 Radiochemical Purity Determination

Determine the radiochemical purity of Technetium Tc 99m Succimer Injection as follows:

1. Activate a 65 × 95-mm silicic acid thin-layer chromatographic (TLC) plate by heating at 100°C to 110°C (212°F to 230°F) for 30 minutes.
2. Cool the TLC plate over silica gel and immediately apply 1 microL of Technetium Tc 99m Succimer Injection about 17 mm from one end of the TLC plate and allow to dry. If necessary, the Technetium Tc 99m Succimer Injection may be diluted with 0.9% sodium chloride injection USP, to a radioactive concentration of 18.5 MBq to 370 MBq (0.5 mCi to 10 mCi) per mL.
3. Develop the TLC plate over a period of about 30 minutes to 45 minutes by ascending chromatography, using a solution of n-butanol saturated with 0.3 N hydrochloric acid (see Note 1). Air-dry the developed TLC Plate.
4. Determine the radioactive distribution on the TLC plate by scanning the chromatogram with a radiochromatographic scanner having a suitably collimated radiation detector.
5. The radioactivity associated with technetium Tc 99m succimer is at Rf between 0.45 and 0.7, hydrolyzed Tc 99m is located at the origin (Rf 0 to 0.15) and the unbound Tc 99m is located at the solvent front (Rf 1)
6. Calculate radiochemical purity using the following formula:
7. Technetium Tc 99m Succimer Injection preparation with not less than 85% radiochemical purity is suitable for administration. Discard preparation with less than 85% radiochemical purity.

Note 1: To prepare the n-butanol saturated with 0.3 N hydrochloric acid solution, place 50 mL of 0.3 N HCl and 50 mL of n-butanol in an Erlenmeyer flask. Place the mixture in an ultrasonic bath for 2 hours, during which time the solution heats up to about 50°C. Cool the solution to room temperature. After about 30 minutes to 45 minutes the phase separation of the mixture will complete. Collect the upper phase of the mixture and discard the lower phase. The solution is stable for up to 7 days when stored at controlled room temperature 20°C to 25°C (68°F to 77°F).

2.6 Administration

Prior to use, visually inspect the prepared Technetium Tc 99m Succimer Injection behind a lead glass shield. Only use solutions that are clear without visible particles.

In making dosage calculations, correction is to be made for radioactive decay. The radioactive half-life of Tc 99m is 6.0 hours.

Using a sterile shielded syringe, aseptically withdraw the prepared Technetium Tc 99m Succimer Injection, and measure the radioactivity in the syringe using a dose calibrator, prior to administration. Ensure that the injected radioactivity is within ±10% of the recommended dose.

Discard unused portion. Handle and dispose radioactive material in accordance with applicable regulations.

2.7 Image Acquisition

The patient should be placed in the prone or supine position, as required by scanning equipment characteristics. Begin image acquisition 1 hour to 4 hours after the intravenous administration of Technetium Tc 99m Succimer Injection.

Delay image acquisition up to 6 hours to 24 hours in patients with severely reduced glomerular filtration rate (eGFR). A specific eGFR threshold at which to delay imaging has not been established [see Warnings and Precautions (5.3)].

2.8 Radiation Dosimetry

The estimated absorbed radiation doses to an average adult and pediatric patients are shown in Table 2.

Table 2 Estimated Radiation Absorbed Dose per Unit of Administered Radioactivity in Selected Organs and Tissues after a Technetium Tc 99m Succimer Injection Dose
Absorbed Dose per Unit of Activity Administered (mGy/MBq)
Organ | Adults | 15 years | 10 years | 5 years | 1 year
Adrenals | 0.012 | 0.016 | 0.024 | 0.035 | 0.06
Bladder wall | 0.018 | 0.023 | 0.029 | 0.031 | 0.057
Bone surface | 0.005 | 0.0062 | 0.0092 | 0.014 | 0.026
Brain | 0.0012 | 0.0015 | 0.0025 | 0.004 | 0.0072
Breasts | 0.0013 | 0.0018 | 0.0028 | 0.0045 | 0.0084
Gall bladder | 0.0083 | 0.01 | 0.014 | 0.022 | 0.031
Stomach wall | 0.0052 | 0.0063 | 0.01 | 0.014 | 0.02
Colon | 0.005 | 0.0063 | 0.01 | 0.014 | 0.024
Intestine | 0.0043 | 0.0055 | 0.0082 | 0.012 | 0.02
Upper large intestine | 0.005 | 0.0064 | 0.095 | 0.014 | 0.023
Lower large intestine | 0.0035 | 0.0043 | 0.0065 | 0.0096 | 0.016
Heart | 0.003 | 0.0038 | 0.0058 | 0.0086 | 0.014
Kidneys | 0.18 | 0.22 | 0.3 | 0.43 | 0.76
Liver | 0.0095 | 0.012 | 0.018 | 0.025 | 0.041
Lungs | 0.0025 | 0.0035 | 0.0052 | 0.008 | 0.015
Muscles | 0.0029 | 0.0036 | 0.0052 | 0.0077 | 0.014
Oesophagus | 0.0017 | 0.0023 | 0.0034 | 0.0054 | 0.0094
Ovaries | 0.0035 | 0.0047 | 0.007 | 0.011 | 0.019
Pancreas | 0.009 | 0.011 | 0.016 | 0.023 | 0.037
Red marrow | 0.0039 | 0.0047 | 0.0068 | 0.009 | 0.014
Skin | 0.0015 | 0.0018 | 0.0029 | 0.0045 | 0.0085
Spleen | 0.013 | 0.017 | 0.026 | 0.038 | 0.061
Testes | 0.0018 | 0.0024 | 0.0037 | 0.0053 | 0.01
Thymus | 0.0017 | 0.0023 | 0.0034 | 0.0054 | 0.0094
Thyroid | 0.0015 | 0.0019 | 0.0031 | 0.0052 | 0.0094
Uterus | 0.0045 | 0.0056 | 0.0083 | 0.011 | 0.019
Remaining organ | 0.0029 | 0.0037 | 0.0052 | 0.0077 | 0.014
Effective Dose per unit of activity administered (mSv/MBq) | 0.0088 | 0.011 | 0.015 | 0.021 | 0.037

3 DOSAGE FORMS AND STRENGTHS

For Injection: NEPHROSCAN contains 1 mg succimer as a white-yellowish to off-white lyophilized powder in a single-dose vial. Upon radiolabeling with technetium Tc 99m, it provides up to 1,480 MBq (40 mCi) Technetium Tc 99m Succimer Injection as a clear, colorless solution in approximately 5 mL volume at calibration date and time.

4 CONTRAINDICATIONS

None

5 WARNINGS AND PRECAUTIONS

5.1 Hypersensitivity Reactions

Hypersensitivity reactions, including urticaria, rash, pruritus, and erythema have been reported with the use of technetium Tc 99m succimer injection in adults and pediatric patients. The time of onset of the reactions varied within 2 hours to several hours after the injection. Have appropriate instruments and medications necessary for immediate treatment of hypersensitivity reactions and monitor patients for reactions during and after administration [see Adverse Reactions (6)].

5.2 Radiation Risks

Technetium Tc 99m succimer injection contributes to a patient's overall long-term cumulative radiation exposure. Long-term cumulative radiation exposure is associated with an increased risk for cancer. Ensure safe handling to minimize radiation exposure to the patient and health care workers. Advise patients to hydrate before and after administration and to void frequently after administration [see Dosage and Administration (2.1, 2.2)].

5.3 Risk in Patients with Advanced Renal Failure

The use of technetium Tc 99m succimer injection in patients with severely reduced estimated glomerular filtration (eGFR) may have an effect on image interpretation as the kidneys may not absorb the technetium Tc 99m succimer and thus the Tc 99m succimer may distribute to organs or parts of the body other than the kidneys. It has been reported that satisfactory images may be obtained in some of these patients by delaying imaging between 6 hours to 24 hours [see Dosage and Administration (2.7)].

6 ADVERSE REACTIONS

The following clinically significant adverse reactions are discussed elsewhere in the labeling:

- Hypersensitivity Reactions [see Warnings and Precautions (5.1)]

The following adverse reactions associated with the use of NEPHROSCAN were identified in clinical studies or postmarketing reports. Because some of these reactions were reported voluntarily from a population of uncertain size, it is not always possible to reliably estimate their frequency or establish a causal relationship to drug exposure.

Immune System Disorders: Hypersensitivity including urticaria, rash, pruritus, and erythema

General Disorders: syncope, fever, and nausea.

8 USE IN SPECIFIC POPULATIONS

8.1 Pregnancy

Risk Summary

Available data with technetium Tc 99m succimer use in pregnant women are insufficient to evaluate for a drug-associated risk of major birth defects and miscarriage. Animal reproduction studies with technetium Tc 99m succimer have not been conducted. Although all radiopharmaceuticals have the potential to cause fetal harm depending on the fetal stage of development and the magnitude of the radiation dose, the radiation exposure to the fetus from technetium Tc 99m succimer is expected to be low (less than 0.50 mGy) (see Data).

The estimated background risk of major birth defects and miscarriage for the indicated population is unknown. All pregnancies have a background risk of birth defects, loss, or other adverse outcomes. In the U.S. general population the estimated background risk of major birth defects and miscarriage in clinically recognized pregnancies are 2% to 4% and 15% to 20%, respectively.

Data

Human Data

No adverse fetal effects of radiation risks have been identified for diagnostic procedures involving less than 50 mGy, which represents less than 10mGy fetal doses.

8.2 Lactation

Risk Summary

Technetium Tc 99m succimer is present in breast milk. There are no data on the effects of technetium Tc 99m succimer on the breastfed infant or the effects on milk production. NEPHROSCAN is used for imaging in infants with renal disease; exposure to technetium Tc 99m succimer via breast milk is expected to be lower. Based on clinical guidelines, exposure of technetium Tc 99m succimer to a breastfed infant may be minimized by advising a lactating woman to temporarily discontinue breastfeeding and to pump and discard breast milk for a minimum of at least 24 hours after administration of Technetium Tc 99m Succimer Injection. The developmental and health benefits of breastfeeding should be considered along with a mother's clinical need for NEPHROSCAN, any potential adverse effects on the breastfed child from technetium Tc 99m succimer or from the underlying maternal condition.

8.4 Pediatric Use

NEPHROSCAN, after radiolabeling with technetium Tc 99m, is indicated for use as an aid in the scintigraphic evaluation of renal parenchymal disorders in pediatric patients, including term neonates. Use of NEPHROSCAN in this age group for this indication is supported by evidence from effectiveness established in adult studies and data from published pediatric studies supporting the safety and effectiveness of weight-based dosing of Technetium Tc 99m Succimer Injection in renal parenchymal imaging in pediatric patients including term neonates [see Dosage and Administration (2.3)].

The recommended amount of radioactivity in pediatric patients, 1.85 MBq/kg (0.05 mCi/kg) with a range of 19 MBq to 74 MBq (0.5 mCi to 2 mCi), is based on published studies that used technetium Tc 99m succimer for the evaluation of acute pyelonephritis, renal scarring, and split renal function in pediatric patients [see Dosage and Administration (2.2)].

Hypersensitivity reactions, including urticaria, rash, pruritus, and erythema have been reported with the use of technetium Tc 99m succimer in pediatric patients [see Warnings and Precautions (5.1) and Adverse Reactions (6)].

8.5 Geriatric Use

Clinical studies of technetium Tc 99m succimer did not include sufficient numbers of subjects 65 years of age and over to determine whether they respond differently from younger patients. Other reported clinical experience has not identified differences in responses between the elderly and younger patients. In general, dose selection for an elderly patient should be cautious usually administering the low end of the dosing range, reflecting the greater frequency of decreased hepatic, renal or cardiac function, and of concomitant disease or other drug therapy.

This drug is known to be substantially excreted by the kidney, and the risk of toxic reactions to this drug may be greater in patients with decreased renal function. Because elderly patients are more likely to have decreased renal function, care should be taken in dose selection, and it may be useful to monitor renal function.

10 OVERDOSAGE

In the event of an overdose of technetium Tc 99m succimer, reduce the radiation absorbed dose to the patient where possible by increasing the elimination of the drug from the body using hydration and frequent bladder voiding. A diuretic might also be considered. If possible, an estimate of the radiation effective dose given to the patient should be made.

11 DESCRIPTION

11.1 Chemical Characteristics

NEPHROSCAN is a sterile, single-dose kit for the preparation of Technetium Tc 99m Succimer Injection a radioactive diagnostic agent, for intravenous use.

The active ingredient, succimer is meso-2,3-dimercaptosuccinic acid with a molecular weight of 182.22 g/mol. The chemical structure of succimer is shown below. Subsequent to radiolabeling with sodium pertechnetate Tc 99m, the active moiety technetium Tc 99m succimer is obtained in situ.

Each vial contains 1 mg succimer, 0.1 mg ascorbic acid, 0.42 mg stannous (tin) chloride dihydrate, 0.02 mg hydrochloric acid and 0.2 mg sodium hydroxide as a white-yellowish to off-white lyophilized powder.

In addition, after radiolabeling with sodium pertechnetate Tc 99m injection, each vial contains up to 1,480 MBq (40 mCi) of technetium Tc 99m succimer in 0.9% sodium chloride injection as a sterile, clear, and colorless solution. pH of the final solution is between 3 and 3.5. FDA approved pH specifications differ from USP.

11.2 Physical Characteristics

Technetium Tc 99m decays by isomeric transition with a physical half-life of 6.02 hours. The principal photon that is useful for detection and imaging studies is listed in Table 3.

Table 3 Principal Radiation Emission Data for Technetium Tc 99m
Radiation/ Emission | Mean % / Disintegration | Mean Energy (keV)
Gamma 2 | 89.07 | 140.5

To correct for physical decay of this radionuclide, the fractions that remain at selected intervals after the time of calibration are shown in Table 4.

Table 4 Physical Decay Chart for Tc 99m, half-life 6.02 hours
Hours | Fraction Remaining | Hours | Fraction Remaining
0 [Calibration time] | 1.000 | 7 | 0.447
1 | 0.891 | 8 | 0.398
2 | 0.794 | 9 | 0.355
3 | 0.708 | 10 | 0.316
4 | 0.631 | 11 | 0.282
5 | 0.562 | 12 | 0.251
6 | 0.501

11.3 External Radiation

The specific gamma ray constant for technetium Tc 99m is 0.78 R/hr-mCi at 1 cm. The first half value layer is 0.017 cm of Pb. To facilitate control of the radiation exposure from millicurie amounts of this radionuclide, the use of a 0.25 cm thickness of Pb will attenuate the radiation emitted by a factor of about 1,000. Table 5 displays the radiation attenuation by lead shielding.

Table 5 Radiation Attenuation by Lead (Pb) Shielding
Shield Thickness (Pb) mm | Coefficient of Attenuation
0.02 | 0.5
0.08 | 0.1
0.16 | 0.01
0.25 | 0.001
0.33 | 0.0001

12 CLINICAL PHARMACOLOGY

12.1 Mechanism of Action

Technetium Tc 99m succimer binds to the cortical region of kidneys and in conjunction with gamma scintigraphy or single photon emission computed tomography (SPECT) is used to image the renal cortices.

12.2 Pharmacodynamics

Technetium Tc 99m succimer only stays bound to viable cortical tissue for >24 hours following administration. The relationship between technetium Tc 99m succimer plasma concentrations and successful imaging is not known.

12.3 Pharmacokinetics

Distribution

Technetium Tc 99m succimer is distributed in the plasma, bound to plasma proteins following intravenous administration. In humans, 53% to 70% of the intravenously administered technetium Tc 99m is protein bound. There is negligible activity in the red blood cells. At 6 hours about 20% of the dose is concentrated in each kidney.

Elimination

Approximately 16% of the technetium Tc 99m succimer activity is excreted in the urine within 2 hours.

13 NONCLINICAL TOXICOLOGY

13.1 Carcinogenesis, Mutagenesis, Impairment of Fertility

No long-term animal studies were performed to evaluate the carcinogenicity potential of technetium Tc 99m succimer.

16 HOW SUPPLIED/STORAGE AND HANDLING

How Supplied

NEPHROSCAN (kit for the preparation of technetium Tc 99m succimer injection), containing 1 mg succimer, is supplied as a white-yellowish to off-white lyophilized powder packaged in a sterile, single-dose vial as a carton of 5 vials (NDC 71083-0020-5).

Storage and Handling

Before radiolabeling, store NEPHROSCAN in a refrigerator at 2°C to 8°C (36°F to 46°F) in original carton. Do not freeze.

After radiolabeling, store Technetium Tc 99m Succimer Injection upright, shielded, for up to 4 hours, at controlled room temperature 20°C to 25°C (68°F to 77°F); excursions permitted to 15°C to 30°C (59°F to 86°F) [see Dosage and Administration (2.4)].

This preparation is approved for use by persons under license by the Nuclear Regulatory Commission or the relevant regulatory authority of an Agreement State.

17 PATIENT COUNSELING INFORMATION

Adequate Hydration

Instruct patients to drink a sufficient amount of water to ensure adequate hydration before their imaging and urge them to drink and urinate as often as possible during the first hours following the administration of Technetium Tc 99m Succimer Injection, in order to reduce radiation exposure [see Dosage and Administration (2.2) and Warnings and Precautions (5.2)].

Lactation

Advise a lactating woman to temporarily discontinue breastfeeding and to pump and discard breast milk for at least 24 hours after Technetium Tc 99m Succimer Injection administration in order to minimize radiation exposure to a breastfed infant [see Use in Specific Populations (8.2)].

Distributed by:
Theragnostics, Inc.
One Broadway
Cambridge, MA 02142
1-617-286-7479

PRINCIPAL DISPLAY PANEL - 1 mg Vial Carton

NEPHROSCAN®
Kit for the Preparation of Technetium Tc 99m Succimer Injection

1 mg per vial Succimer

For intravenous use only after radiolabeling with
Sodium Pertechnetate Tc 99m Injection, USP

THERAGNOSTICS

NDC:71083-0020-5
Rx Only
5 Single-Dose Vials. Discard Unused Portion